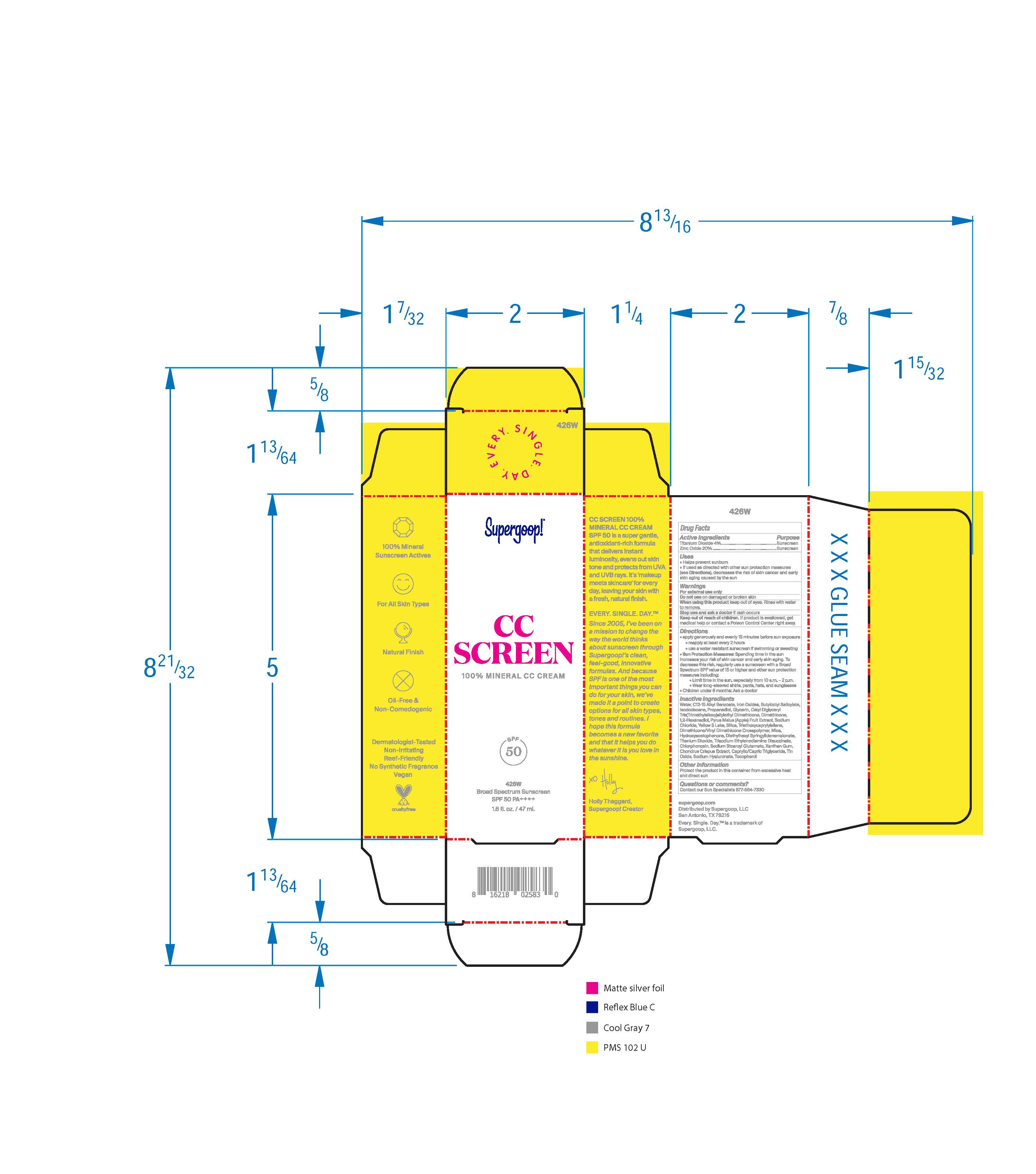 DRUG LABEL: CC Screen 100% Mineral CC Cream Broad Spectrum SPF 50 426W
NDC: 75936-239 | Form: CREAM
Manufacturer: Supergoop, LLC
Category: otc | Type: HUMAN OTC DRUG LABEL
Date: 20241206

ACTIVE INGREDIENTS: ZINC OXIDE 20 g/100 mL; TITANIUM DIOXIDE 4 g/100 mL
INACTIVE INGREDIENTS: ISODODECANE; GLYCERIN; .BETA.-TOCOPHEROL; CHLORPHENESIN; XANTHAN GUM; PROPANEDIOL; ALKYL (C12-15) BENZOATE; SILICON DIOXIDE; MICA; FERRIC OXIDE YELLOW; WATER; BUTYLOCTYL SALICYLATE; 1,2-HEXANEDIOL; DIMETHICONE/VINYL DIMETHICONE CROSSPOLYMER (SOFT PARTICLE); APPLE; SODIUM CHLORIDE; MEDIUM-CHAIN TRIGLYCERIDES; STANNIC OXIDE; HYALURONATE SODIUM; DIETHYLHEXYL SYRINGYLIDENEMALONATE; HYDROXYACETOPHENONE; TRIETHOXYCAPRYLYLSILANE; FERRIC OXIDE RED; TRISODIUM ETHYLENEDIAMINE DISUCCINATE; CHONDRUS CRISPUS CARRAGEENAN

CC Screen 100% Mineral CC Cream Broad Spectrum SPF 50 426W

Active Ingredients Purpose

Titanium Dioxide 4% Sunscreen

Zinc Oxide 20% Sunscreen

Uses

- Helps Prevent Sunburn
- If used as directed with other sun protection measures (see Directions), decreases the risk of skin cancer and early skin aging caused by the sun.

Keep out of reach of children. If product is swallowed, get medical help or contact a poison Control Center right away.

Stop use and ask a doctor if rash occurs or rash occurs

Warnings

- For external use only
- Do not use on damaged or broken skin
- When using this product keep out of eyes. Rinse with water to remove.

Directions

- apply generously and evenly 15 minutes before sun exposure
- reapply at least every 2 hours.
- use a water-resistant sunscreen if swimming or sweating

Sun Protection Measures Spending time in the sun increases your risk of skin cancer and early skin aging. To decrease this risk, regularly use a sunscreen with a Broad-Spectrum SPF value of 15 or higher and other sun protection measures including:

• limit your time in the sun, especially from 10 a.m. – 2 p.m.

• wear long-sleeved shirts, pants, hats, and sunglasses

•children under 6 months of age: ask a doctor.

Inactive Ingredients

Water, C12-15 Alkyl Benzoate, Iron Oxides, Butyloctyl Salicylate, Isododecane, Propanediol, Glycerin, Cetyl Diglyceryl Tris(Trimethylsiloxy)silylethyl Dimethicone, Dimethicone, 1,2-Hexanediol, Pyrus Malus (Apple) Fruit Extract, Sodium Chloride, Yellow 5 Lakes, Silica, Triethoxycaprylylsilane, Dimethicone/Vinyl Dimethicone Crosspolymer, Mica, Hydroxyacetophenone, Diethylhexyl Syringlidenemalonate, Titanium Dioxide, Trisodium Ethylenediamine Disuccinate, Chlorphenesin, Xanthan Gum, Chrondrus Crispus Extract, Caprylic/Capric Triglyceride, Tin Oxide, Sodium Hyaluronate, Tocopherol

PACKAGE LABEL

CC Screen

100% Mineral CC Cream 426W

SPF 50

Broad Spectrum SPF 50 PA+++

1.6 fl. oz./ 47 ml.